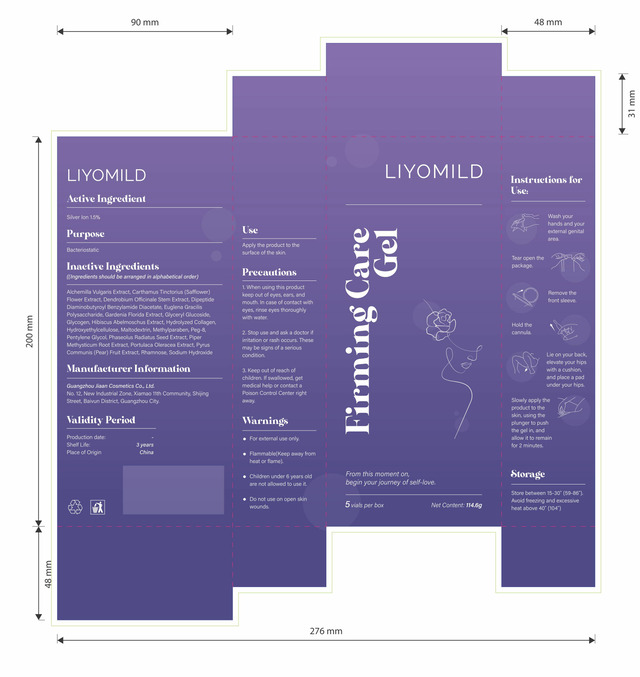 DRUG LABEL: Firming Care Gel
NDC: 85349-001 | Form: GEL
Manufacturer: Guangzhou Jiaan Cosmetics Co.,Ltd.
Category: otc | Type: HUMAN OTC DRUG LABEL
Date: 20250415

ACTIVE INGREDIENTS: SILVER CATION 1.5 g/100 g
INACTIVE INGREDIENTS: DENDROBIUM OFFICINALE STEM; METHYLPARABEN; WATER; PEG-8; RHAMNOSE; PENTYLENE GLYCOL; GLYCERYL GLUCOSIDE; PURSLANE; PIPER METHYSTICUM ROOT; MUNG BEAN; ALCHEMILLA VULGARIS FLOWERING TOP; GLYCOGEN; DIPEPTIDE DIAMINOBUTYROYL BENZYLAMIDE DIACETATE; MALTODEXTRIN; HYDROXYETHYLCELLULOSE; SODIUM HYDROXIDE; PYRUS COMMUNIS (PEAR) FRUIT

85349-001
Firming Care Gel

Active Ingredient(s)

SILVER ION 1.5%

Purpose

Bacteriostatic

Use

Apply the product to the surface of the skin.

Warnings

● For external use only.
● Flammable(Keep away fron heat or flame).
● Children under 6 years old are not allowed to use it.
● Do not use on open skin wounds.

Do not use on open skin wounds.

When using this product keep out of eyes, ears, and mouth. In case of contact with
eyes, rinse eyes thoroughly with water.

Stop use and ask a doctor if irritation or rash occurs, These may be signs of a serious condition.

Keep out of reach of children. If swallowed, get medical help or contact a
Poison Control Center right away.

Directions

1. Wash your hands and your external genital area.

2. Tear open the package.

3. Remove the front sleeve.

4. Hold the cannula.
5. Lie on your back, elevate your hips with a cushion, and place a pad under your hips.
6. Slowly apply the product to the skin, using the plunger to push the gel in, and allow it to remain for 2 minutes.

Other information

Store between 15-30" (59-86). Avoid freezing and excessive
heat above 40° (104")

Inactive ingredients

Alchemilla Vulgaris Extract, Carthamus Tinctorius (Safflower) Flower Extract, Dendrobium Officinale Stem Extract, Dipeptide
Diaminobutyroy| Benzylamide Diacetate, Euglena Gracilis Polysaccharide, Gardenia Florida Extract, Glyceryl Glucoside,
Glycogen, Hibiscus Abelmoschus Extract, Hydrolyzed Collagen, Hydroxyethylcellulose, Maltodextrin, Methylparaben, Peg-8,
Pentylene Glycol, Phaseolus Radiatus Seed Extract, Piper Methysticum Root Extract, Portulaca Oleracea Extract, Pyrus
Communis (Pear) Fruit Extract, Rhamnose, Sodium Hydroxide